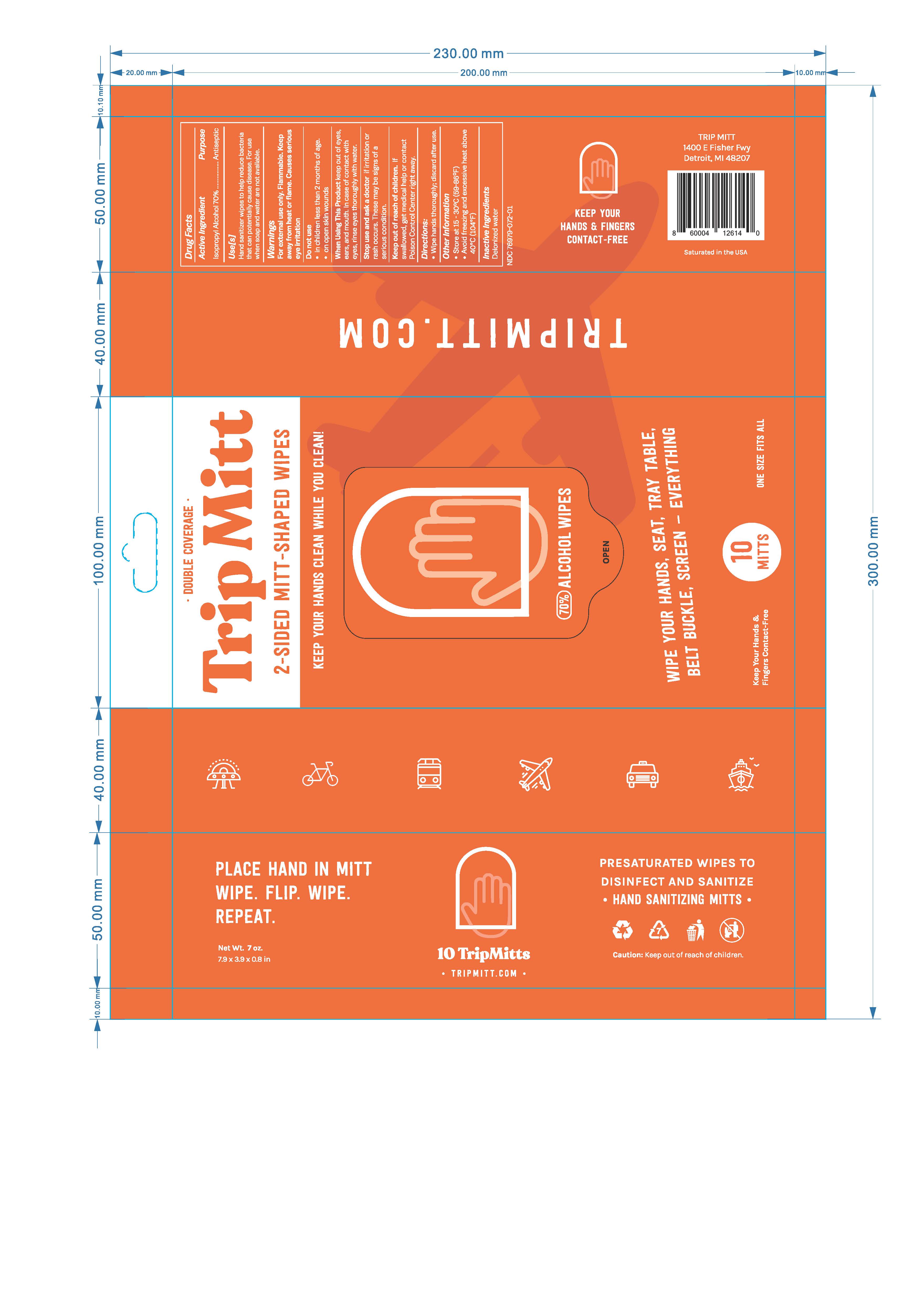 DRUG LABEL: Trip Mitt
NDC: 76979-072 | Form: CLOTH
Manufacturer: Trip Wipes LLC
Category: otc | Type: HUMAN OTC DRUG LABEL
Date: 20201106

ACTIVE INGREDIENTS: ISOPROPYL ALCOHOL 70 mL/100 mL
INACTIVE INGREDIENTS: WATER

Active Ingredient(s)

Isopropyl Alcohol 70% v/v. Purpose: Antiseptic

Purpose

Antiseptic

Use

Hand Sanitizer wipes to help reduce bacteria that potentially can cause disease. For use when soap and water are not available.

Warnings

For external use only. Flammable. Keep away from heat or flame. Causes serious eye irritation.

Do not use

- in children less than 2 months of age
- on open skin wounds

When using this product keep out of eyes, ears, and mouth. In case of contact with eyes, rinse eyes thoroughly with water.
Stop use and ask a doctor if irritation or rash occurs. These may be signs of a serious condition.
Keep out of reach of children. If swallowed, get medical help or contact a Poison Control Center right away.

Stop use and ask a doctor if irritation or rash occurs. These may be signs of a serious condition.

Keep out of reach of children. If swallowed, get medical help or contact a Poison Control Center right away.

Directions

- Wipe hands thoroughly, discard after use.

Other information

- Store between 15-30C (59-86F)
- Avoid freezing and excessive heat above 40C (104F)

Inactive ingredients

deionized water

Package Label - Principal Display Panel

000 ml NDC: 76979-072-01